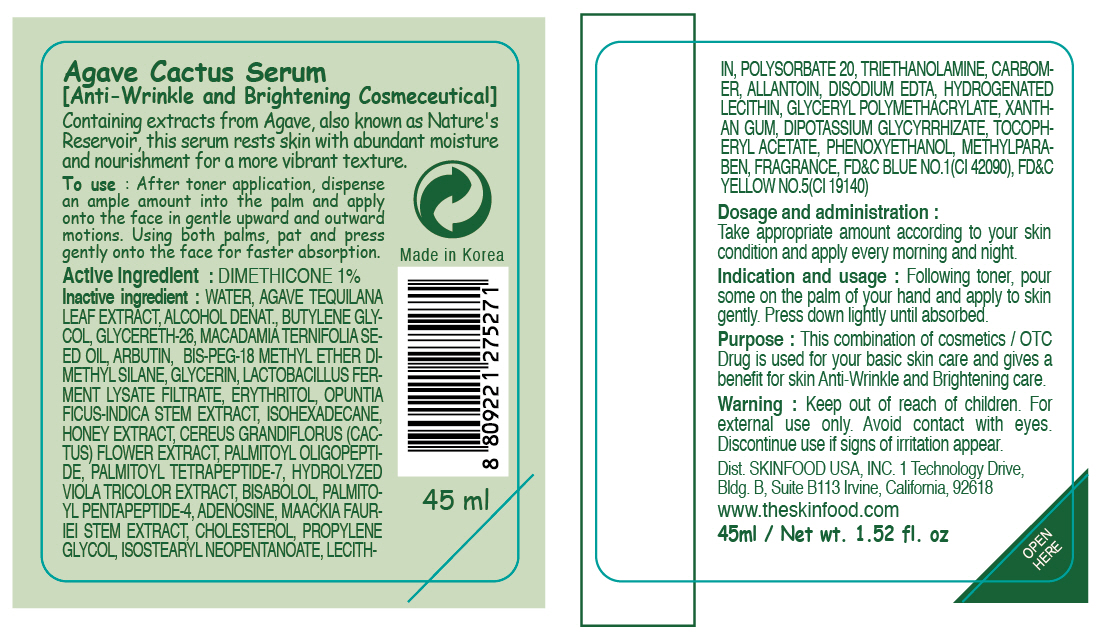 DRUG LABEL: AGAVE CACTUS SERUM
NDC: 76214-003 | Form: CREAM
Manufacturer: SKINFOOD CO., LTD.
Category: otc | Type: HUMAN OTC DRUG LABEL
Date: 20110721

ACTIVE INGREDIENTS: DIMETHICONE 0.45 mL/45 mL
INACTIVE INGREDIENTS: WATER; AGAVE TEQUILANA LEAF; BUTYLENE GLYCOL; GLYCERETH-26; MACADAMIA OIL; ARBUTIN; GLYCERIN; ERYTHRITOL; HONEY; OPUNTIA FICUS-INDICA STEM; ISOHEXADECANE; MAACKIA FLORIBUNDA STEM; METHYLPARABEN; PHENOXYETHANOL; TROLAMINE; POLYSORBATE 20; ALLANTOIN; PALMITOYL OLIGOPEPTIDE; LECITHIN, SOYBEAN; PALMITOYL TETRAPEPTIDE-7; PALMITOYL PENTAPEPTIDE-4; ADENOSINE; HYDROGENATED SOYBEAN LECITHIN; EDETATE DISODIUM; PROPYLENE GLYCOL; CHOLESTEROL; XANTHAN GUM

Drug Facts

Active ingredient: DIMETHICONE

Inactive ingredients:

WATER, AGAVE TEQUILANA LEAF EXTRACT, ALCOHOL DENAT., BUTYLENE GLYCOL, GLYCERETH-26, MACADAMIA TERNIFOLIA SEED OIL, ARBUTIN, BIS-PEG-18 METHYL ETHER DIMETHYL SILANE, GLYCERIN, LACTOBACILLUS FERMENT LYSATE FILTRATE, ERYTHRITOL, OPUNTIA FICUS-INDICA STEM EXTRACT, ISOHEXADECANE, HONEY EXTRACT, CEREUS GRANDIFLORUS (CACTUS) FLOWER EXTRACT, PALMITOYL OLIGOPEPTIDE, PALMITOYL TETRAPEPTIDE-7, HYDROLYZED VIOLA TRICOLOR EXTRACT, BISABOLOL, PALMITOYL PENTAPEPTIDE-4, ADENOSINE, MAACKIA FAURIEI STEM EXTRACT, CHOLESTEROL, PROPYLENE GLYCOL, ISOSTEARYL NEOPENTANOATE, LECITHIN, POLYSORBATE 20, TRIETHANOLAMINE, CARBOMER, ALLANTOIN, DISODIUM EDTA, HYDROGENATED LECITHIN,GLYCERYL POLYMETHACRYLATE, XANTHAN GUM, DIPOTASSIUM GLYCYRRHIZATE, TOCOPHERYL ACETATE, PHENOXYETHANOL, METHYLPARABEN, FRAGRANCE

Purpose:

This combination of cosmetics is used for your basic skin care and gives a benefit for skin Anti-Wrinkle and Brightening care.

Warnings:

For external use only. Avoid contact with eyes. Discontinue use if signs of irritation appear.

Keep out of reach of children:

Keep out of reach of children.

Indication and usage:

Following toner, pour some on the palm of your hand and apply to skin gently. Press down lightly until absorbed.

Dosage and administration:

Take appropriate amount according to your skin condition and apply every morning and night.